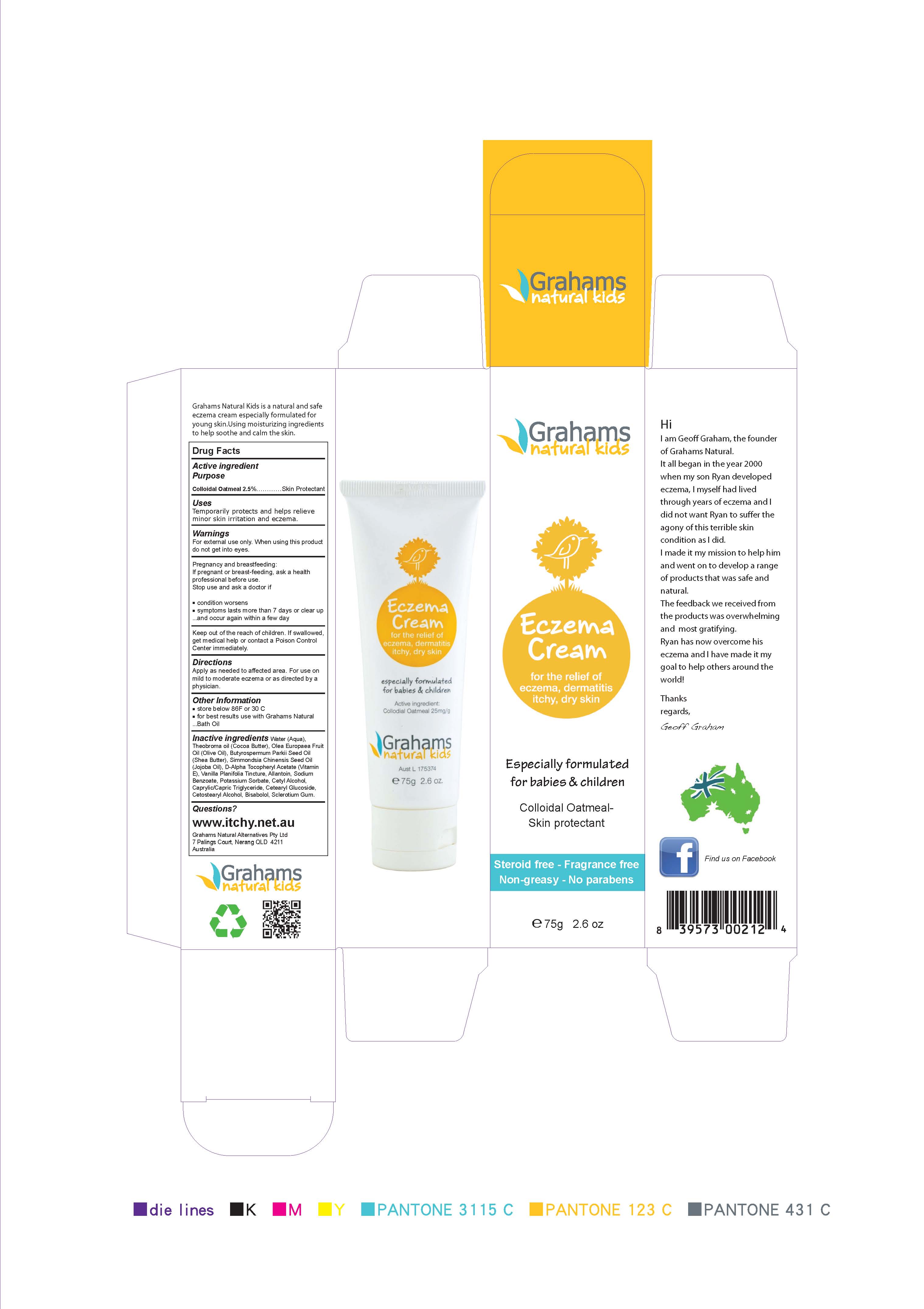 DRUG LABEL: GN Kids Eczema
                
NDC: 42387-123 | Form: CREAM
Manufacturer: Grahams Natural Alternatives Pty Ltd
Category: otc | Type: HUMAN OTC DRUG LABEL
Date: 20120813

ACTIVE INGREDIENTS: OATMEAL 25 mg/1 g
INACTIVE INGREDIENTS: WATER; COCOA BUTTER; OLIVE OIL; SHEANUT OIL; JOJOBA OIL; .ALPHA.-TOCOPHEROL, D-; VANILLA; ALLANTOIN; SODIUM BENZOATE; POTASSIUM SORBATE; CETYL ALCOHOL; MEDIUM-CHAIN TRIGLYCERIDES; CETEARYL GLUCOSIDE; CETOSTEARYL ALCOHOL; LEVOMENOL; BETASIZOFIRAN

DRUG FACTS

ACTIVE INGREDIENT

COLLOIDAL OATMEAL

Keep Out Of Reach Of Children.
If swallowed,get medical help or contact a Poison Control Center immediately.

PURPOSE

Eczema Cream. For external use only.

INDICATIONS AND USAGE

Eczema cream, apply to affected area.

DOSAGE AND ADMINISTRATION

Topical cream. Apply as needed to affected areas.

WARNINGS

For External use only. When using this product do not get into eyes.

If pregnant or breastfeeding, ask a professional before use.

Stop use and ask doctor if conditions worsen, symptoms last more than 7days or clear up and occur again in a few days.

INACTIVE INGREDIENT

Water,Theobroma Oil, Olea Europaea Fruit Oil, Vitellaria Paradoxa, Simmondsia Chimensis Seed Oil, D-Alpha Tocopheryl Acetate,Vanilla Planifolia tincture, Allantoin, Sodium Benzoate, Potassium Sorbate, Cetyl Alcohol, Capryllic/Capric Triglyceride,Cetearyl Glucoside, Cetostearyl Alcohol, Bisabolol, Sclerotium Gum.

PACKAGE LABEL

image of box